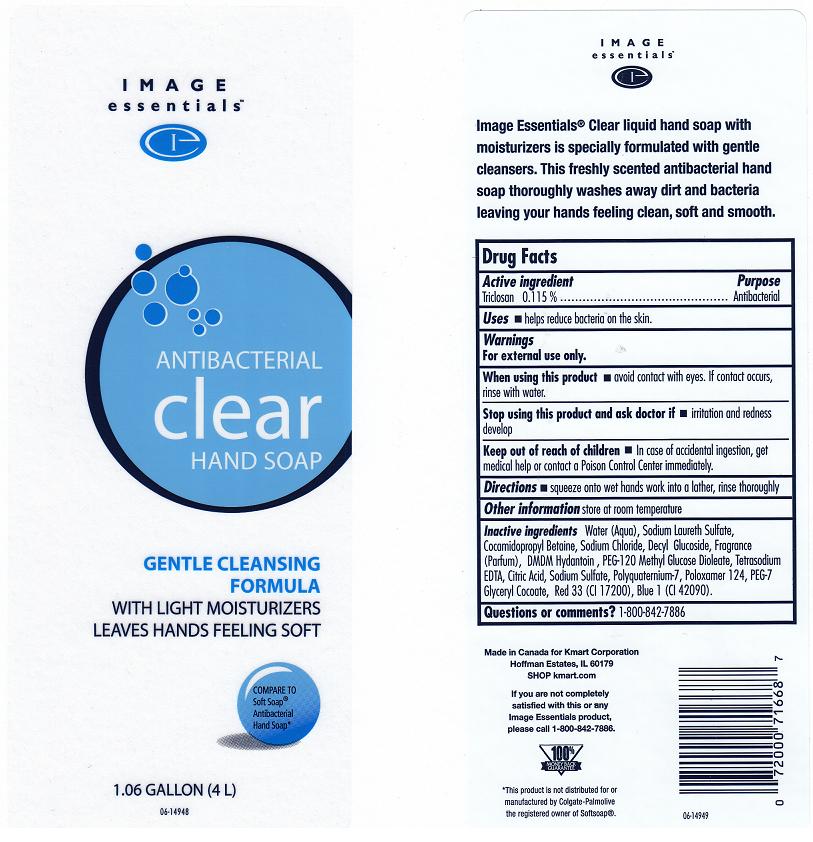 DRUG LABEL: IMAGE ESSENTIALS
NDC: 49738-721 | Form: LIQUID
Manufacturer: KMART CORPORATION
Category: otc | Type: HUMAN OTC DRUG LABEL
Date: 20120224

ACTIVE INGREDIENTS: TRICLOSAN 0.115 mL/100 mL
INACTIVE INGREDIENTS: WATER; SODIUM LAURETH SULFATE; COCAMIDOPROPYL BETAINE; SODIUM CHLORIDE; DECYL GLUCOSIDE; DMDM HYDANTOIN; PEG-120 METHYL GLUCOSE DIOLEATE; EDETATE SODIUM; CITRIC ACID MONOHYDRATE; SODIUM SULFATE; POLYQUATERNIUM-7 (70/30 ACRYLAMIDE/DADMAC; 1600 KD); POLOXAMER 124; PEG-7 GLYCERYL COCOATE; D&C RED NO. 33; FD&C BLUE NO. 1

DRUG FACTS

ACTIVE INGREDIENT

TRICLOSAN 0.115%

PURPOSE

ANTIBACTERIAL

USES

HELPS REDUCE BACTERIA ON THE SKIN.

WARNINGS

FOR EXTERNAL USE ONLY.

WHEN USING THIS PRODUCT

AVOID CONTACT WITH EYES. IF CONTACT OCCURS, RINSE WITH WATER.

STOP USING THIS PRODUCT AND ASK DOCTOR IF

IRRITATION AND REDNESS DEVELOP.

KEEP OUT OF REACH OF CHILDREN

IN CASE OF ACCIDENTAL INGESTION, GET MEDICAL HELP OR CONTACT A POISON CONTROL CENTER IMMEDIATELY.

DIRECTIONS

SQUEEZE ONTO WET HANDS, WORK INTO A LATHER, RINSE THOROUGHLY.

OTHER INFORMATION

STORE AT ROOM TEMPERATURE.

INACTIVE INGREDIENTS

WATER (AQUA), SODIUM LAURETH SULFATE, COCAMIDOPROPYL BETAINE, SODIUM CHLORIDE, DECYL GLUCOSIDE, FRAGRANCE (PARFUM), DMDM HYDANTOIN, PEG-120 METHYL GLUCOSE DIOLEATE, TETRASODIUM EDTA, CITRIC ACID, SODIUM SULFATE, POLYQUATERNIUM-7, POLOXAMER 124, PEG-7 GLYCERYL COCOATE, RED 33 (CI 17200), BLUE 1 (CI 42090).

QUESTIONS OR COMMENTS?

1-800-842-7886